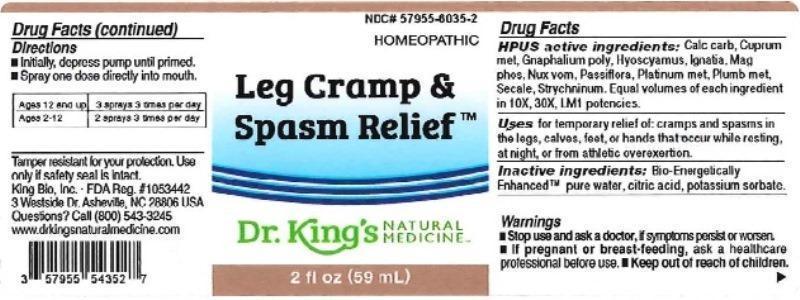 DRUG LABEL: Leg Cramp and Spasm Relief
NDC: 57955-6035 | Form: LIQUID
Manufacturer: King Bio Inc.
Category: homeopathic | Type: HUMAN OTC DRUG LABEL
Date: 20160322

ACTIVE INGREDIENTS: OYSTER SHELL CALCIUM CARBONATE, CRUDE 10 [hp_X]/59 mL; COPPER 10 [hp_X]/59 mL; PSEUDOGNAPHALIUM OBTUSIFOLIUM 10 [hp_X]/59 mL; HYOSCYAMUS NIGER 10 [hp_X]/59 mL; STRYCHNOS IGNATII SEED 10 [hp_X]/59 mL; MAGNESIUM PHOSPHATE, DIBASIC TRIHYDRATE 10 [hp_X]/59 mL; STRYCHNOS NUX-VOMICA SEED 10 [hp_X]/59 mL; PASSIFLORA INCARNATA FLOWERING TOP 10 [hp_X]/59 mL; PLATINUM 10 [hp_X]/59 mL; LEAD 10 [hp_X]/59 mL; CLAVICEPS PURPUREA SCLEROTIUM 10 [hp_X]/59 mL; STRYCHNINE 10 [hp_X]/59 mL
INACTIVE INGREDIENTS: WATER; ANHYDROUS CITRIC ACID; POTASSIUM SORBATE

Leg Cramps & Spasm Relief™

ACTIVE INGREDIENT

Drug Facts__________________________________________________________________________________________________________

HPUS active ingredients: Calcarea carbonica, Cuprum metallicum, Gnaphalium polycephalum, Hyoscyamus niger, Ignatia amara, Magnesia phosphorica, Nux vomica, Passiflora incarnata, Platinum metallicum, Plumbum metallicum, Secale cornutum, Strychninum. Equal volumes of each ingredient in 10X, 30X, and LM1 potencies.

INDICATIONS AND USAGE

Uses for temporary relief of: cramps and spasms in the legs, calves, feet, or hands that occur while resting, at night, or from athletic overexertion.

Inactive Ingredients:

Bio-Energetically Enhanced™ pure water, citric acid and potassium sorbate.

Warnings

- Stop use and ask a doctor if symptoms persist or worsen.
- If pregnant or breast-feeding, ask a healthcare professional before ues.

- Keep out of reach of children.

Directions

- Initially, depress pump until primed.
- Spray one dose directly into mouth.
- Ages 12 and up: 3 sprays 3 times per day.
- Ages 2-12: 2 sprays 3 times per day.

OTHER SAFETY INFORMATION

Tamper resistant for your protection. Use only if safety seal is intact.

PURPOSE

Uses for temporary relief of:

- cramps and spasms in the legs, calves, feet, or hands that occur while resting, at night, or from athletic overexertion.